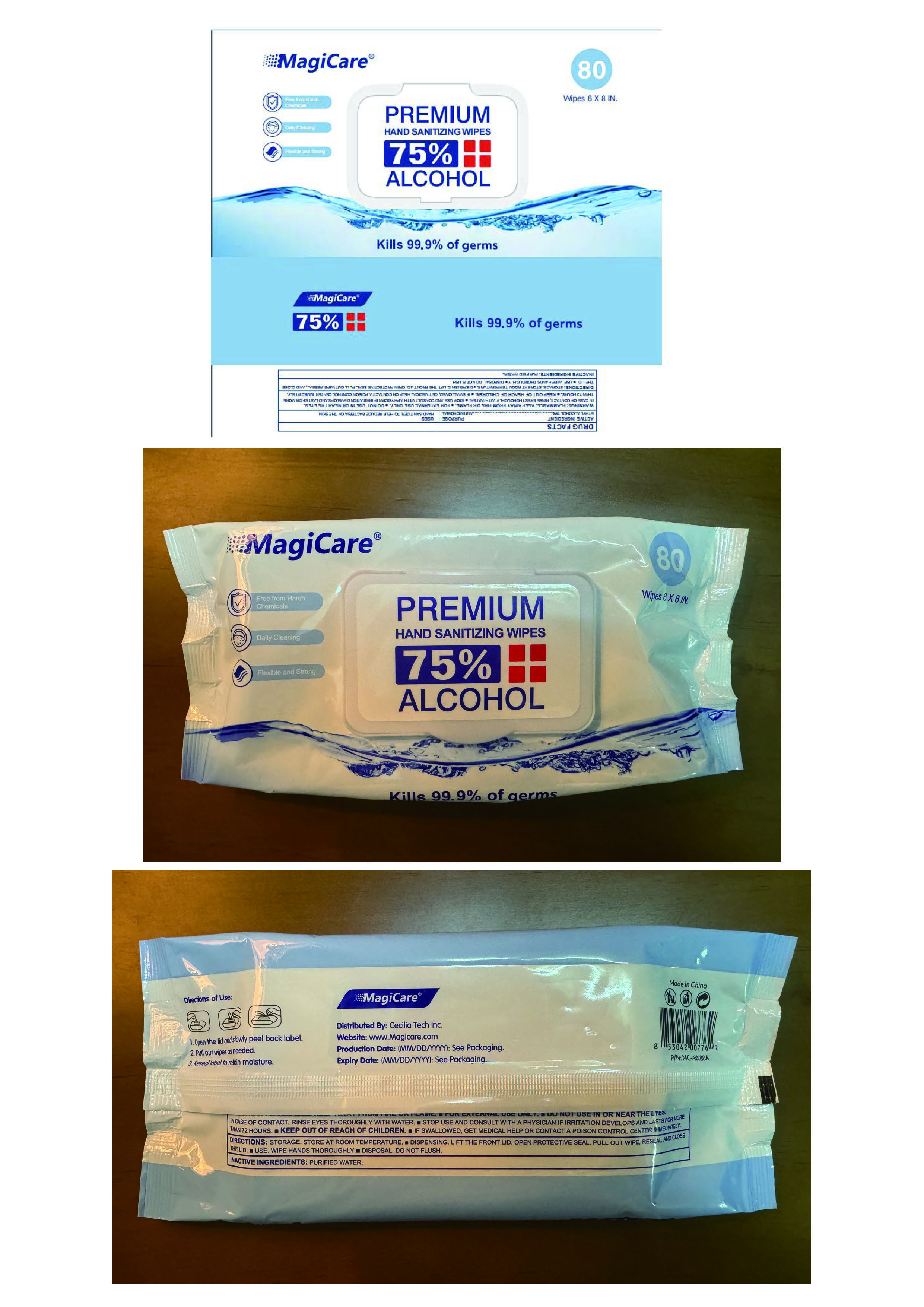 DRUG LABEL: Alcohol Wipes
NDC: 77665-104 | Form: CLOTH
Manufacturer: Guangzhou Baihua Co., Ltd.
Category: otc | Type: HUMAN OTC DRUG LABEL
Date: 20250521

ACTIVE INGREDIENTS: ALCOHOL 75 mL/100 mL
INACTIVE INGREDIENTS: GLYCERIN; HYDROGEN PEROXIDE; WATER

Alcohol Wipes

Purpose

PURPOSE: ANTIMICROBIAL

Active Ingredient(s)

ACTIVE INGREDIENT: Alcohol 75%

Use

USES: HAND SANITIZER TO HELP REDUCE BACTERIA ON THE SKIN.

Warnings

WARNINGS: FLAMMABLE. KEEP AWAY FROM FIRE OR FLAME

■ FOR EXTERNAL USE ONLY.

■ DO NOT USE IN OR NEAR THE EYES.

IN CASE OF CONTACT, RINSE EYES THOROUGHLY WITH WATER.

■ STOP USE AND CONSULT WITH A PHYSICIAN IF IRRITATION DEVELOPS AND LASTS FOR MORE THAN 72 HOURS.

■ KEEP OUT OF REACH OF CHILDREN.

■ IF SWALLOWED, GET MEDICAL HELP OR CONTACT A POISON CONTROL CENTER IMMEDIATELY.

■ DO NOT USE IN OR NEAR THE EYES.

WHEN USING

IN CASE OF CONTACT, RINSE EYES THOROUGHLY WITH WATER.

■ IF SWALLOWED, GET MEDICAL HELP OR CONTACT A POISON CONTROL CENTER IMMEDIATELY

■ STOP USE AND CONSULT WITH A PHYSICIAN IF IRRITATION DEVELOPS AND LASTS FOR MORE THAN 72 HOURS

■ KEEP OUT OF REACH OF CHILDREN

Directions

■ DISPENSING. LIFT THE FRONT LID. OPEN PROTECTIVE SEAL. PULL OUT WIPE, RESEAL, AND CLOSE THE LID.

■ USE. WIPE HANDS THOROUGHLY.

■ DISPOSAL. DO NOT FLUSH.

Directions of Use:
1. Open the lid and slowly peel back label.2. Pull out wipes as needed.
3. Reseal label to retain moisture.

Other information

STORAGE. STORE AT ROOM TEMPERATURE.

Inactive ingredients

Glycerol, Hydrogen Peroxide, RO pure water

Package Label - Principal Display Panel

Alcohol Wipes(80pcs) 77665-104-01